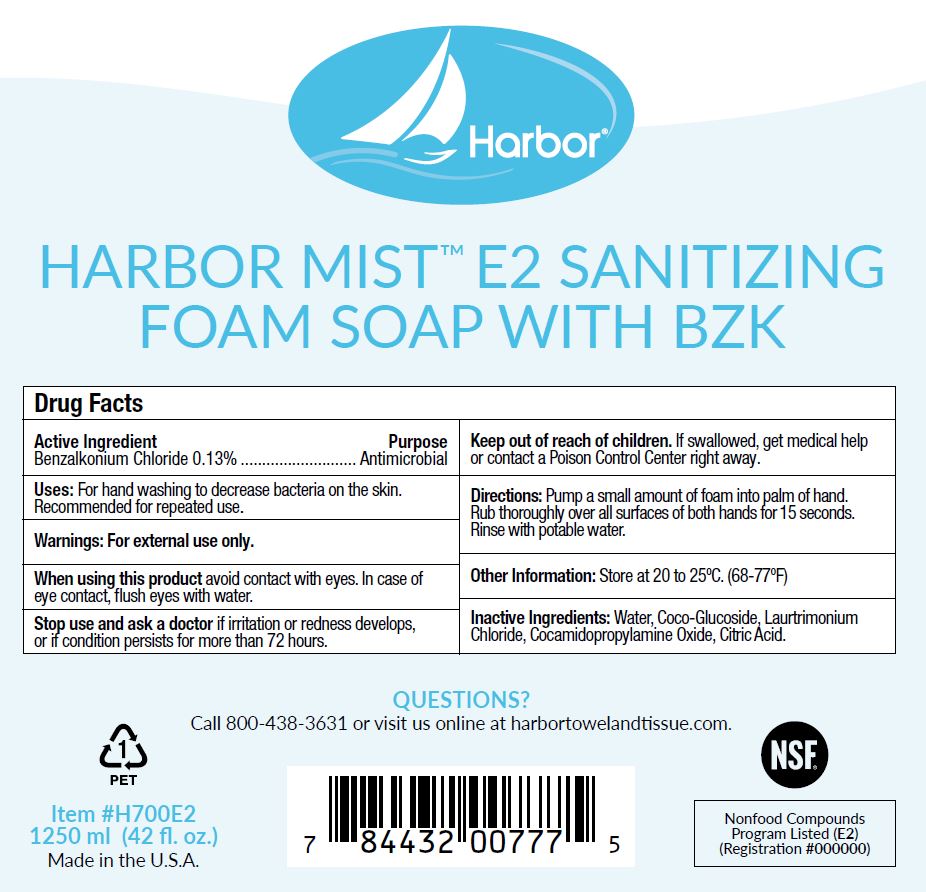 DRUG LABEL: Harbor Mist E2 Sanitizing Foam with BZK
NDC: 81792-004 | Form: LIQUID
Manufacturer: Von Drehle Corporation
Category: otc | Type: HUMAN OTC DRUG LABEL
Date: 20241125

ACTIVE INGREDIENTS: BENZALKONIUM CHLORIDE 1.3 mg/1 mL
INACTIVE INGREDIENTS: WATER; COCO GLUCOSIDE; CITRIC ACID MONOHYDRATE; LAURTRIMONIUM CHLORIDE; COCAMIDOPROPYLAMINE OXIDE

Harbor Mist E2 Sanitizing BZK - 81792-004

Active Ingredient

Benzalkonium Chloride 0.13%

Purpose

Antimicrobial

Uses:

For hand washing to decrease bacteria on the skin.

Recommended for repeated use.

Warnings:

For external use only.

When using this productavoid contact with eyes.

In case of eye contact, flush eyes with water.

Stop use and ask a doctorif irritation or redness develops, or if condition persists for more than 72 hours.

Keep out of reach of children.

If swallowed, get medical help or contact a Poison Control Center right away.

Directions:

Pump a small amount of foam into palm of hand.

Rub thoroughly over all surfaces of both hands for 15 sec.

Rinse with potable water.

Other Information:

Store at 20 to 25 C (68-77 F)

Inactive ingredients:

Water, Coco-Glucoside, Lautrimonoium Chloride, Cocamidopropylamine Oxide, Citric Acid.

PACKAGE LABEL

Harbor

HARBOR MIST E2 SANITIZING

FOAM SOAP WITH BZK

Manufactured for von Drehle Corporation I Hickory, NC 28601

QUESTIONS?

Call 800-438-3631 or visit us online at harbortowelandtissue.com.

NSF

Nonfood Compounds

Program listed (E2)

(Registration #000000)

1

PET

Item #H700E2

1250 ml (42 fl. oz.)

Made in the U.S.A.